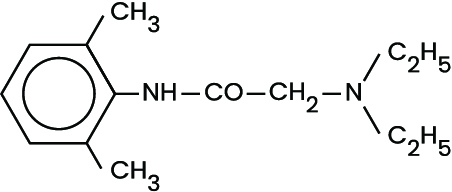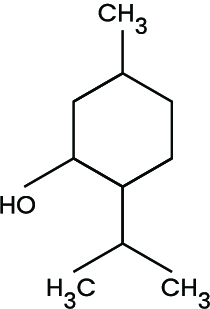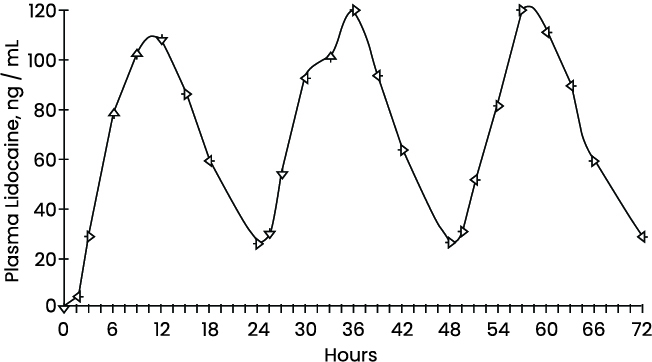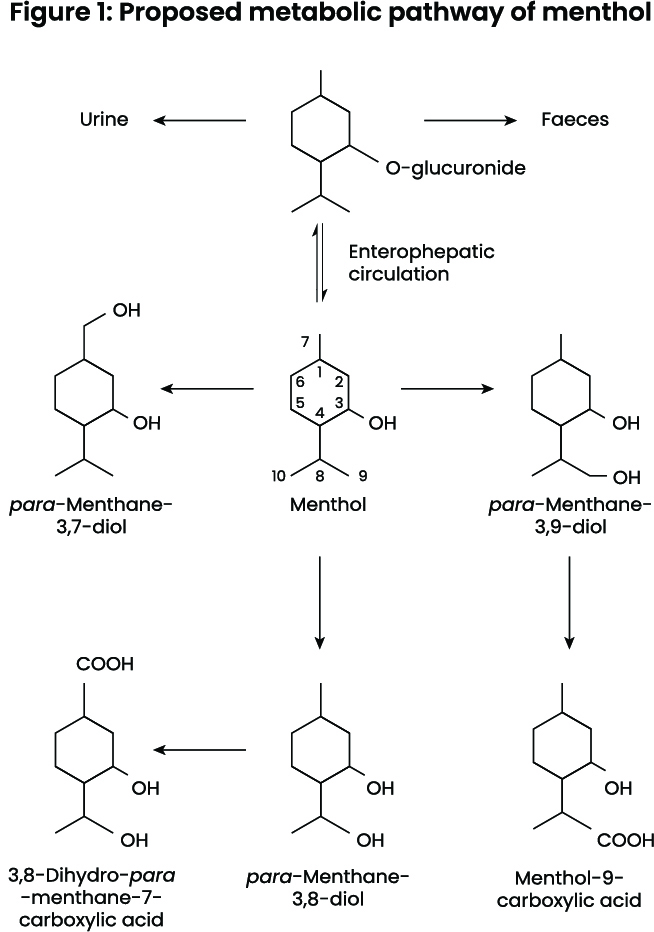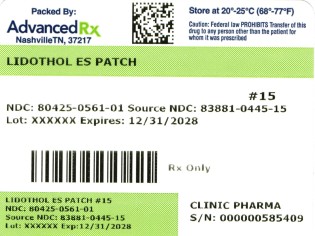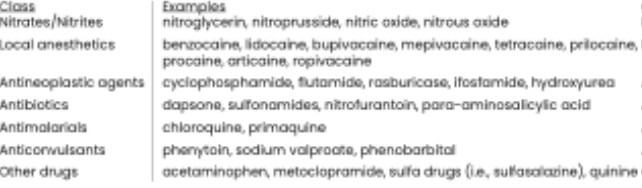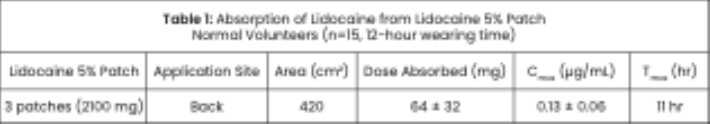 DRUG LABEL: Lidothol ES
NDC: 80425-0561 | Form: SYSTEM
Manufacturer: Advanced Rx of Tennessee, LLC
Category: prescription | Type: HUMAN PRESCRIPTION DRUG LABEL
Date: 20260202

ACTIVE INGREDIENTS: LIDOCAINE 0.056 g/1 g; MENTHOL 0.07 g/1 g
INACTIVE INGREDIENTS: BUTYL ACRYLATE/C16-C20 ALKYL METHACRYLATE/METHACRYLIC ACID/METHYL METHACRYLATE COPOLYMER; .ALPHA.-TOCOPHEROL

Lidothol ES

PATIENT INFORMATION

Lidocaine 4%, Menthol 5% Drug-in-Adhesive System

For External Use Only

Do not use:

• on the face or rashes, wounds or damaged skin

• in the eyes, mouth, or other mucous membranes

• on genitals

• with a heating pad

• right before or after heart surgery

• any Lidothol® ES from a pouch that has not been applied immediately after opening the pouch

• in large quantities, particularly over raw surfaces or blistered areas

• if the pouch is broken or torn

• more than 2 Lidothol® ES per day unless directed by a doctor

• children under 18 years of age

Ask a doctor before use if you have:

• allergies to topical or external products

• high blood pressure, heart disease, or kidney disease

When using this product:

• avoid contact with eyes. If eye contact occurs, rinse thoroughly with water

• the risk of heart attack or stroke may increase if you use more than directed or for longer than directed

Stop use and ask doctor ifthe condition worsens, or if symptoms persist for more than 7 days or clear up and occur again within a few days.

If pregnant or breastfeeding, ask a health professional before use.Do not use during the last 3 months of pregnancy, as it may cause problems in the unborn child or complications during delivery.

Keep out of reach of children.If ingested, seek medical help or contact a Poison Control Center 1-800-222-1222 immediately. Dispose of used Lidothol® ES by folding the sticky ends together.

Lidothol® ES Patient Information

Before you begin using this medication, read this entire patient information sheet. If you have any questions, please consult your physician or pharmacist. Inform your physician if your condition does not improve or if it worsens. This information may not include all of the details needed to use Lidothol® ES safely and effectively. Discuss use with your doctor or pharmacist.

What is Lidothol® ES?

A drug-in-adhesive system consisting of the external anesthetic lidocaine (4%) and the external analgesic menthol (5%).

What is Lidothol® ES used for?

Lidothol® ES assists patients in the management of mild to moderate acute pain or mild to moderate aches. Lidothol® ES is applied to the skin at the specific region experiencing these pain symptoms. The synthesis of lidocaine and menthol is a highly effective combination of pain relievers working to alleviate discomfort while the root cause is being managed and treated by your healthcare providers.

What are the possible side effects with Lidothol® ES?

• Common: itching or redness of the skin following application

• Note: The majority of patients experience no significant adverse events following system application. Serious side effects are, in general, related to accidental toxicity of medication by applying considerably more than directed by your doctor or pharmacist or by ingesting the contents of Lidothol® ES.

• Tell your healthcare provider about all the medicines you take. This includes prescription and nonprescription medicines, vitamins, and herbal supplements.

• Avoid excessive alcohol usage, since it may increase the potential for Central Nervous System (CNS) effects such as dizziness, confusion, lightheadedness, and orthostatic hypotension.

This is not a complete list of possible side effects. For more information, talk with your doctor or pharmacist. You may report side effects to the FDA at 1-800-FDA-1088 or www.fda.gov/medwatch.

Warnings

Do not use:

• on wounds, cuts, damaged or infected skin

• on eyes, mouth, genitals, or other mucous membranes

• children under 18 years of age

• if you are allergic to any of the ingredients in this product

Stop use and call your healthcare provider right away if you experience any of the following warning signs or any other unusual symptoms of concern:

• if pain worsens

• pale, gray, or blue colored skin (cyanosis)

• rapid heart rate

• shortness of breath

• lightheadedness

• fatigue

• swelling or numbness of the tongue or throat

• severe headache or vomiting

• dizziness or faintness

• changes in vision or speech

Directions for Use

Adults 18 years and older:

• clean and dry the affected area

• using scissors, carefully cut the pouch along the dotted line to open the pouch and remove Lidothol® ES

• remove the transparent release liner before applying Lidothol® ES to the skin

• apply one Lidothol® ES to the affected area of pain and leave it in place for 8 to 12 hours

• if pain persists after using the first Lidothol® ES, a second Lidothol® ES may be applied for up to another 8 to 12 hours

• use only one Lidothol® ES at a time

• Lidothol® ES may be cut into smaller sizes with scissors prior to removing the release liner

• safely discard the used Lidothol® ES (whole or cut pieces) where children and pets cannot get to them

• wash hands with soap and water after applying or removing Lidothol® ES

General information for safe and effective use of Lidothol® ES

Do not use this product for another indication. Do not give this drug to anyone else, even if they have the same condition. This product is intended for use as prescribed by a physician.

How should I store Lidothol® ES?

Store at 68–77 ºF (20–25 ºC); excursions permitted to 59–86 °F (15–30 °C). Keep away from heat or sunlight. Protect from excessive moisture. Safely discard the product after the expiration date posted on the product label. Discard Lidothol® ES away from small children or animals.

DO NOT use the product after the expiration date printed on the box.

The insert provides the most important information about Lidothol® ES. If you would like more information, talk with your healthcare provider or pharmacist. Additional information for healthcare professionals can be found in the following sections.

What are the active ingredients in Lidothol® ES?

Lidothol® ES consists of lidocaine 4% and menthol 5%.

What are the inactive ingredients in Lidothol® ES?

Acrylate copolymer PSA adhesives, alpha-tocopherol (vitamin E)

Description:

Lidothol® ES is a prescription drug-in-adhesive system, packaged with 15 systems:

1 per pouch, 15 pouches. Lidocaine is present in a 4% concentration (w/w). It is chemically designated as 2-(diethylamino)-N-(2,6-dimethylphenyl) acetamide and has an empirical formula of C14H22N2O. The molecular weight of lidocaine is 234.34 g/mol. Menthol is present in a 5% concentration (w/w). The chemical name is (1R,2S,5R)-2-isopropyl-5-methylcyclohexanol. The empirical formula for menthol is C10H20O with a molecular weight of 156.27 g/mol.

Lidothol® ES consists of a Drug-in-Adhesive System containing lidocaine 4% and menthol 5%, applied to flexible woven polyester backing and protected by a plastic film. The protective film is removed prior to application to the skin. The size of the system is 10 cm x 14 cm.

Lidocaine is chemically designated as 2-(diethylamino)-N-(2,6-dimethylphenyl) acetamide, has an octanol: water partition ratio of 43 at pH 7.4, and has the following structure:

Menthol is chemically designated as 2-Isopropyl-5-methylcyclohexanol. It contains colorless, hexagonal crystals, usually needle-like; fused masses or crystalline powder with a pleasant, peppermint-like odor. It has a melting point between 31°C to 36°C. Menthol has the following structure:

Each system contains:Lidocaine: 373.5 mg (45 mg per gram adhesive) in an anhydrous base. Menthol: 415 mg (50 mg per gram adhesive) in an anhydrous base. It also contains the following inactive ingredients: acrylate copolymer PSA adhesives, alpha-tocopherol (vitamin E)

INDICATIONS AND USAGE

Lidothol® ES is a formulation used to assist patients in the treatment of mild to moderate acute or chronic aches or pain. Muscle or joint pain can be due to muscle or ligament strains, simple backache, tendonitis, osteoarthritis, rheumatoid arthritis, peripheral neuropathies such as diabetic neuropathy or post-herpetic neuralgia, and other complex regional pains. It can also be used to help with certain types of headaches, but use with caution when applying in order to avoid eye contact. Other uses may be considered if deemed clinically relevant.

DOSAGE AND ADMINISTRATION

Apply Lidothol® ES to intact skin to cover the most painful area. Apply no more than two systems per day. Each system should not be applied for more than 12 hours in a given 24-hour period. Lidothol® ES may be cut into smaller sizes with scissors prior to the removal of the protective film. Clothing may be worn over the area of application. Smaller treatment areas are recommended for debilitated patients or those with impaired elimination. If irritation or a burning sensation occurs during application, remove the system and do not reapply until the irritation subsides. When Lidothol® ES is used concurrently with other products containing local anesthetic agents, the amount absorbed from all formulations must be considered.

CONTRAINDICATIONS

Lidothol® ES is contraindicated in patients with a known history of sensitivity to local anesthetics of the amide type, or to any other component of the product.

WARNINGS AND PRECAUTIONS

Excessive dosage or short intervals between doses can result in high plasma levels and serious adverse effects. Patients should be instructed to strictly adhere to the recommended dosage and administration guidelines set forth in this literature and on their prescription label. The management of serious adverse reactions may require the use of resuscitative equipment, oxygen, or other resuscitative drugs.

Methemoglobinemia

Cases of methemoglobinemia have been reported in association with local anesthetic use. Although all patients are at risk for methemoglobinemia, patients with glucose-6-phosphate dehydrogenase deficiency, congenital or idiopathic methemoglobinemia, cardiac or pulmonary compromise, infants under 6 months of age, and concurrent exposure to oxidizing agents or their metabolites are more susceptible to developing clinical manifestations of the condition. If local anesthetics must be used in these patients, close monitoring for symptoms and signs of methemoglobinemia is recommended.

Signs and symptoms of methemoglobinemia may occur immediately or may be delayed for some hours after exposure and are characterized by cyanotic skin discoloration and abnormal coloration of the blood. Methemoglobin levels may continue to rise; therefore, immediate treatment is required to avert more serious central nervous system and cardiovascular adverse effects, including seizures, coma, arrhythmias, and death.

Discontinue Lidothol® ES and any other oxidizing agents. Depending on the severity of the symptoms, patients may respond to supportive care, i.e., oxygen therapy, hydration. More severe symptoms may require treatment with methylene blue, exchange transfusion, or hyperbaric oxygen.

Accidental Exposure in Children

Even a used Lidothol® ES contains a large amount of lidocaine. The potential exists for a small child or a pet to suffer serious adverse effects from chewing or ingesting a new or used Lidothol® ES. However, the risk with this formulation has not been evaluated. It is important for patients to store and dispose of Lidothol® ES beyond the reach of children, pets, and others. (See HANDLING AND DISPOSAL)

Excessive Dosing

Excessive dosing by applying Lidothol® ES to larger areas for longer than the recommended wearing time could result in increased absorption of lidocaine and high blood concentrations, leading to serious adverse effects. Lidocaine toxicity could be expected at lidocaine blood concentrations above 5 µg/mL. The rate of systemic absorption and elimination determines the blood concentration of lidocaine. Longer duration of application, application of more than the recommended number of systems, smaller patients, or impaired elimination may all contribute to increasing the blood concentration of lidocaine. With recommended dosing of Lidothol® ES, the average blood concentration is about 0.13 µg/mL, but concentrations higher than 0.25 µg/mL have been observed in some patients.

Sedation and Impaired Alertness

Because of the possibility of sedation, patients should be cautioned regarding the use of heavy machinery or automobiles, or any activities made hazardous by decreased alertness.

Hepatic Disease

Patients with severe hepatic disease are at greater risk of developing toxic blood concentrations of lidocaine, because of their inability to metabolize lidocaine normally.

Allergic Reactions

Patients allergic to para-aminobenzoic acid derivatives (procaine, tetracaine, benzocaine, etc.) have not shown cross-sensitivity to lidocaine. However, Lidothol® ES should be used with caution in patients with a history of drug sensitivities, especially if the etiologic agent is uncertain. Allergic and anaphylactoid reactions associated with lidocaine, although rare, can occur. They are characterized by angioedema, bronchospasm, dermatitis, dyspnea, hypersensitivity, laryngospasm, pruritus, shock, and urticaria. If they occur, consult your doctor.

Non-intact Skin

Although not tested, application to broken or inflamed skin may result in higher blood concentrations of lidocaine from increased absorption. Lidothol® ES is only recommended for use on intact skin.

Eye Exposure

The contact of Lidothol® ES with the eyes, although not studied, should be avoided based on the findings of severe eye irritations with the use of similar products in animals. If eye contact occurs, immediately wash out the eye with water or saline and protect the eye until sensation returns.

External Heat Sources

Placement of external heat sources, such as heating pads or electric blankets, over Lidothol® ES is not recommended, as this has not been evaluated and may increase plasma lidocaine levels.

ADVERSE REACTIONS

The most common adverse reactions occur at the application site, including dermatitis, itching, or scaling. These tend to be dose-limiting and diminish with time. Serious adverse experiences following the administration of Lidothol® ES are similar in nature to those observed in other amide local anesthetic-containing agents. These adverse experiences are, in general, dose-related and may result from high plasma levels caused by excessive dosage, rapid absorption, or may result from hypersensitivity, idiosyncrasy, or a diminished tolerance on the part of the patient. Serious adverse experiences are generally systemic in nature. During or immediately after treatment with Lidothol® ES, the skin at the site of application may develop redness, blisters, bruising, burning sensation, depigmentation, dermatitis, or mild irritation.

DRUG INTERACTIONS

Antiarrhythmic Drugs

Lidothol® ES should be used with caution in patients receiving Class 1 antiarrhythmic drugs (such as tocainide and mexiletine) since the toxic effects are additive and potentially synergistic.

Local Anesthetics

When Lidothol® ES is used concurrently with other products containing local anesthetic agents, the amount absorbed from all formulations must be considered.

Methemoglobinemia

Patients that are administered local anesthetics may be at increased risk of developing methemoglobinemia when concurrently exposed to the following oxidizing agents:

a

USE IN SPECIFIC POPULATIONS

Pregnancy

The safety of Lidothol® ES has not been established during pregnancy. There are no well-controlled studies in pregnant women. Discuss with a physician prior to using Lidothol® ES during pregnancy.

Lactation

The effect of Lidothol® ES on breastfed infants has not been evaluated. Lidothol® ES has not been studied during lactation. Discuss with a physician prior to using Lidothol® ES while breastfeeding.

Pediatric/Geriatric Use

Safety and effectiveness in pediatric and geriatric patients have not been established.

OVERDOSAGE

There have been no reports of overdosage with Lidothol® ES. Signs of overdosage would include vomiting, drowsiness, coma, respiratory depression, and seizures. In the case of overdosage, discontinue the product immediately, treat the patient symptomatically, and institute supportive measures.

CLINICAL PHARMACOLOGY

Pharmacodynamics

Menthol works by targeting the κ-opioid receptor on the TRPM8 neuron. The TRPM8 neuron is normally activated at temperatures between 46.4–82.4 °F (8–28 °C). Menthol causes the neuron to fire at temperatures above normal activation, which triggers the characteristic cooling sensation. Also, because of menthol’s specific targeting of the κ-opioid receptor, it is endowed with analgesic properties.

Lidocaine is an amide-type local anesthetic agent and is suggested to stabilize neuronal membranes by inhibiting the ionic fluxes required for the initiation and conduction of impulses.

The penetration of lidocaine into intact skin after application of Lidothol® ES is sufficient to produce an analgesic effect, but less than the amount necessary to produce a complete sensory block.

Pharmacokinetics

Absorption

The amount of lidocaine and menthol systemically absorbed is directly related to both the duration of application and the surface area over which it is applied. In a pharmacokinetic study, three lidocaine 5% patches were applied over an area of 420 cm² of intact skin on the back of normal volunteers for 12 hours. Blood samples were withdrawn for a determination of lidocaine concentration during the application and for 12 hours after the removal of the patches.

The results are summarized in Table 1: When lidocaine 5% patch is used according to the recommended dosing instructions, only 3 ± 2% of the dose applied is expected to be absorbed.

At least 95% (665 mg) of lidocaine will remain in a used patch. The mean peak blood concentration of lidocaine is about 0.13 µg/mL (about 1/10 of the therapeutic concentration required to treat cardiac arrhythmias).

Repeated application of three days indicated that the lidocaine concentration does not increase with daily use. The mean plasma pharmacokinetic profile for the 15 healthy volunteers is shown in Figure 1.

Figure 1

Mean lidocaine blood concentrations after three consecutive daily applications of three lidocaine patches simultaneously for 12 hours per day in healthy volunteers (n =15).

Distribution

When lidocaine is administered intravenously to healthy volunteers, the volume of distribution is 0.7 to 2.7 L/kg (mean 1.5 ± 0.6 SD, n= 15). At concentrations produced by application of lidocaine patch 5%, lidocaine is approximately 70% bound to plasma proteins, primarily alpha-1-acid glycoprotein. At much higher plasma concentrations (1 to 4µg/mL of free base), the plasma protein binding of lidocaine is concentration dependent. Lidocaine crosses the placental and blood-brain barriers, presumably by passive diffusion.

Metabolism

It is not known if lidocaine is metabolized in the skin. Lidocaine is metabolized rapidly by the liver to a number of metabolites, including monoethylglycinexylidide (MEGX) and glycinexylidide (GX), both of which have pharmacologic activity similar to, but less potent than that of lidocaine. A minor metabolite, 2,6-xylidine, has unknown pharmacologic activity but is carcinogenic in rats. The blood concentration of this metabolite is negligible following application of lidocaine patch 5%. Following intravenous administration, MEGX and GX concentrations in serum range from 11% to 36% and from 5% to 11% of lidocaine concentrations, respectively.

Humans rapidly metabolize menthol primarily in the liver by the microsomes, using the enzyme CYP2A6. Cytochrome P450-mediated oxidation occurs in humans, yielding various alcohol and hydroxy acid derivatives. These are eliminated in the urine unchanged or conjugated with glucuronic acid.

Excretion

Lidocaine and its metabolites are excreted by the kidneys. Less than 10% of lidocaine is excreted unchanged. The half-life of lidocaine elimination from plasma following IV administration is 81 to 149 minutes (mean 107 ± 22 SD, n=15). The systemic clearance is 0.33 to 0.90 L/min (mean 0.64 ± 0.18 SD, n=15).

Menthol is largely eliminated as glucuronides. In an experiment, 79% of a 1g (Quick, 1928) and 78% of a 10-20 mg (Aitz et al., 1972) oral dose of menthol was eliminated as the glucuronic acid conjugate within 6 h after administration to volunteers. Of a dose of 47 mg/kg body weight [3-3H]-(-)-menthol, 62% was eliminated in the urine 17 hours after administration.

Smaller amounts were distributed in the feces and ileum; only 1% of the activity remained in the liver (Clegg et al., 1982).

NONCLINICAL TOXICOLOGY

Carcinogenesis

A minor metabolite, 2,6-xylidine, has been found to be carcinogenic in rats. The blood concentration of metabolite is negligible following application of Lidothol® ES.

Mutagenesis

Lidocaine is not mutagenic in Salmonella/mammalian microsome test nor clastogenic in chromosome aberration assay with human lymphocytes and mouse micronucleus test.

Impairment of Fertility

The effect of Lidothol® ES on fertility has not been studied.

HOW SUPPLIED

Lidothol ES is supplied in the following dosage form:
15 Systems: 1 per pouch, 15 pouches | NDC 80425-0561-01

STORAGE

Store at 68–77 °F (20–25 °C); excursions permitted to 59–86 °F (15–30 °C). Keep away from heat or sunlight. Protect from excessive moisture. The product can be considered safe and effective to use when maintained under these recommended conditions within the posted expiration date.

HANDLING AND DISPOSAL

Wash hands immediately after applying or removing Lidothol® ES. Eye contact with Lidothol® ES should be avoided. Do not store the system outside the pouch. Apply immediately after removal from the protective film. Fold used systems so the adhesive side sticks to itself, then safely discard used systems or pieces of cut systems where children and pets cannot access them. Lidothol® ES should be kept out of reach of children.